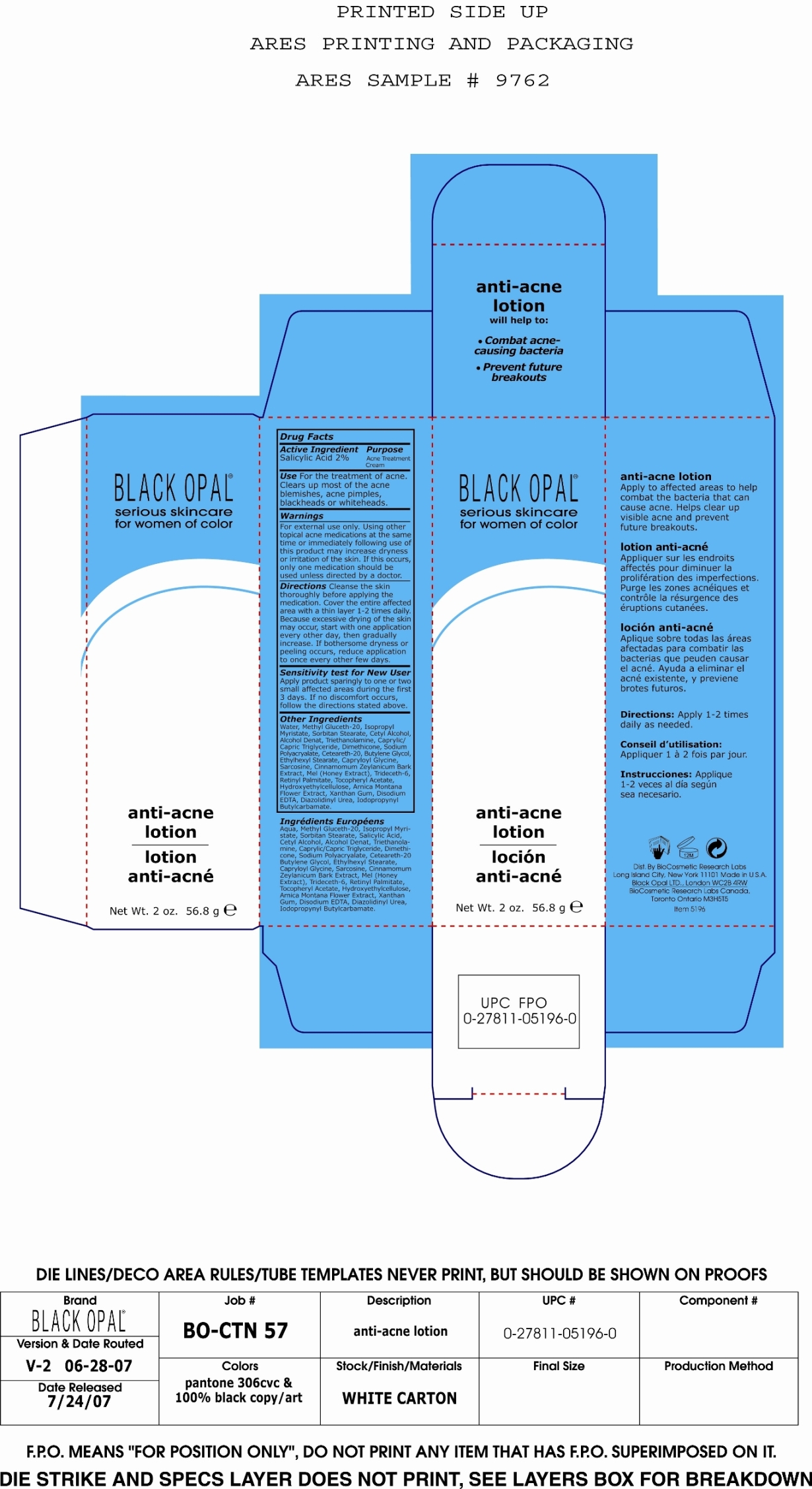 DRUG LABEL: Anti-acne
NDC: 59735-312 | Form: LOTION
Manufacturer: Biocosmetics Research Labs
Category: otc | Type: HUMAN OTC DRUG LABEL
Date: 20080123

ACTIVE INGREDIENTS: Salicylic Acid 2 g/100 g

Anti-acne Lotion

Active Ingredient:

Salicylic Acid 2%

Purpose:

Acne Treatment Cream

INDICATIONS AND USAGE

Use:For the treatment of acne. Clears up most of the acne blemishes, acne pimples, blackheads or whiteheads.

Warnings:

For external use only.

Using other topical acne medications at the same time or immediately following use of this product may increase dryness or irritation of the skin. If this occurs, only one medication should be used unless directed by a doctor.

Directions:
Cleanse the skin thoroughly before applying the medication. Cover the entire affected area with a thin layer 1-2 times daily. Because excessive drying of the skin may occur, start with one application every other day, then gradually increase. If bothersome dryness or peeling occurs, reduce application to once every other few days.

PRECAUTIONS

Sensitivity test for new user:

Apply product sparingly to one or two small affected areas during the first 3 days. If no discomfort occurs, follow the directions stated above.

INACTIVE INGREDIENT

Other Ingredients:

Water, Methyl Gluceth-20, Isopropyl Myristate, Sorbitan Stearate, Cetyl Alcohol, Alcohol Denat, Triethanolamine, Caprylic/Capric Triglyceride, Dimethicone,
Sodium Polyacrylate, Ceteareth-20, Butylene Glycol, Ethylhexyl Stearate, Capryloyl Glycine, Sarcosine, Cinnamomum Zeylanicum Bark Extract, Mel (Honey Extract), Trideceth-6, Retinyl Palmitate, Tocopheryl Acetate, Hydroxyethylcellulose, Arnica Montana Flower Extract, Xanthan Gum, Disodium EDTA, Diazolidinyl Urea, Iodopropynyl Butylcarbamate.